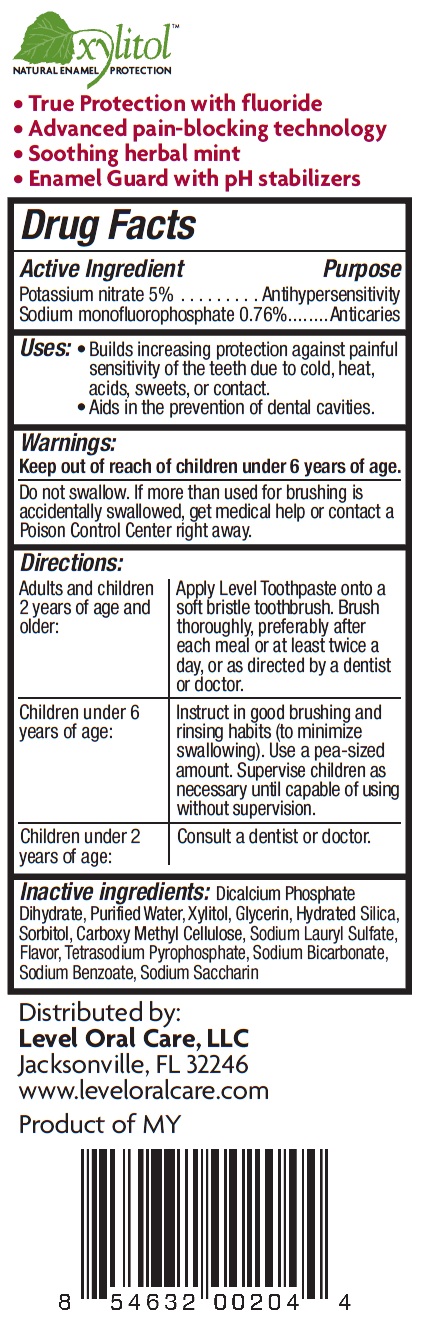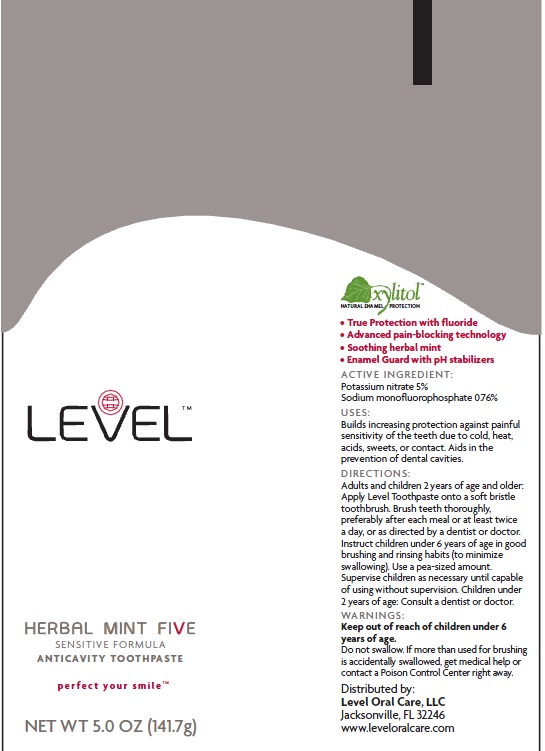 DRUG LABEL: LEVEL HERBAL MINT FIVE SENSITIVE FORMULA ANTICAVITY
NDC: 50001-131 | Form: PASTE
Manufacturer: LEVEL ORAL CARE, LLC
Category: otc | Type: HUMAN OTC DRUG LABEL
Date: 20110509

ACTIVE INGREDIENTS: POTASSIUM NITRATE 5 g/100 g; SODIUM MONOFLUOROPHOSPHATE 0.76 g/100 g
INACTIVE INGREDIENTS: WATER; XYLITOL; GLYCERIN; HYDRATED SILICA; SORBITOL; SODIUM LAURYL SULFATE; SODIUM PYROPHOSPHATE; SODIUM BICARBONATE; SODIUM BENZOATE; SACCHARIN SODIUM

LEVEL HERBAL MINT FIVE SENSITIVE FORMULA ANTICAVITY TOOTHPASTE perfect your smile

DRUG FACTS

Active Ingredient Purpose

Potassium Nitrate 5% Antihypersensitivity

Sodium Monofluorophosphate 0.76%....Anticaries

Purpose:
Antihypersensitivity and Anticaries

Uses:

Builds increasing protection against painful sensitivity of the teeth due to cold, heat acids, sweets, or contact

Aids in the prevention of dental cavities.

WARNINGS

Do not swallow. If more than used for brushing is accidentally swallowed, get medical help or contact a Poison control Center right away.

Keep out of reach of children under 6 years of age.

DIRECTIONS

Adults and children 2 years of age and older:

Apply Level Toothpaste on to a soft bristle toothbrush. Brush thoroughly, preferably after each meal or at least twice a day or as directed by a dentist or doctor

Children under 6 years of age

Instruct in good brushing and rinsing habits (to minimize swallowing). Use a pea-sized amount. Supervise children as necessary until capable of using without supervision.

Children under 2 years of age:

consult a dentist or doctor

Inactive Ingredients

Dicalcium Phosphate Dihydrate, Purified WAter, Xylitol, Glycerin, Hydrated Silica, Sorbitol, Carboxy Methyl Cellulose, Sodium Lauryl sulfate, Flavor, Tetrasodium Pyrophosphate, Sodium Bicarbonate, Sodium Benzoate, Sodium Saccharin

Xylitol

Natural Enamel protection

True protection with fluoride

Advanced pain-blocking technology

Soothing herbal mint

enamel guard with pH stabilizers

Distributed by

level oral care, LLC

Jacksonville, FL 32246

www.leveloralcare.com

Product of MY

PACKAGE LABEL

Level

Herbal Mint Five

Sensitive Formula

Anticavity Toothpaste

perfect your smile

NET WT. 5.0 OZ (141.7G)

Xylitol

natural enamel protection

True protection with fluoride

Advanced pain-blocking technology

Soothing herbal mint

Enamel Guard with pH stabilizers

ACTIVE INGREDIENT:

Potassium nitrate 5%

Sodium monofluorophosphate 0.76%

USES:

Builds increasing protection against painful sensitivity of the teeth due to cold heat acids, sweets or contact. Aids in the prevention of dental cavities

DIRECTIONS:

Adults and children 2 years of age and older: Apply Level Toothpaste onto a soft bristle toothbrush. Brush teeth thoroughly, preferably after each meal or at least twice a day, or as directed by a dentist or doctor. Instruct children under 6 years of age in good brushing and rinsing habits (to minimize swallowing). Use a pea-sized amount. supervise children as necessary until capable of using without supervision. Children under 2 years of age: Consult a dentist or doctor

WARNINGS

Keep out of reach of children under 6 years of age. Do not swallow. if more than used from brushing is accidentally swallowed, get medical help or contact a Poison Control Center right away.

Distributed by:

Level Oral Care, LLC
Jacksonville, FL 32246
www.leveloralcare.com